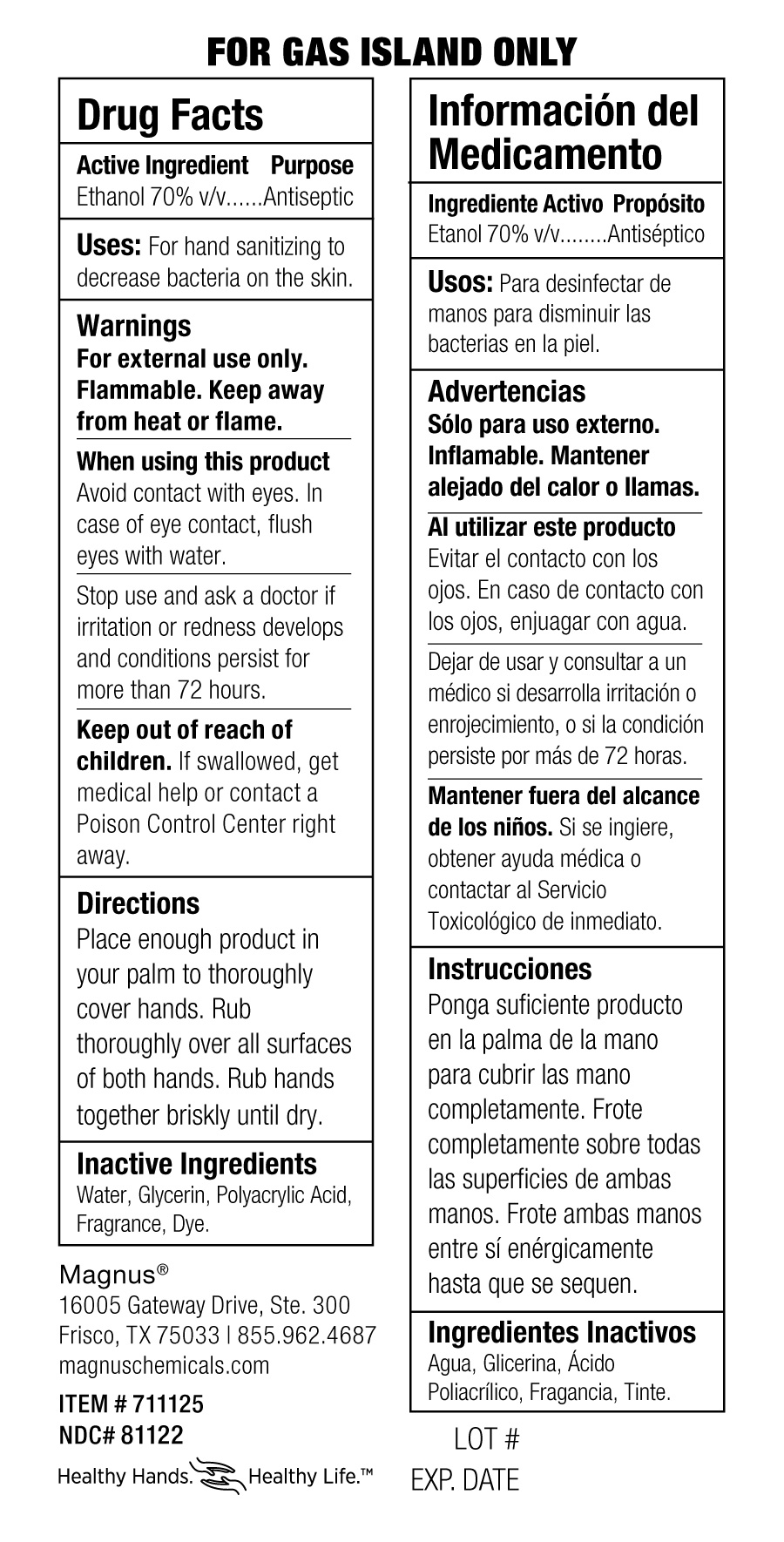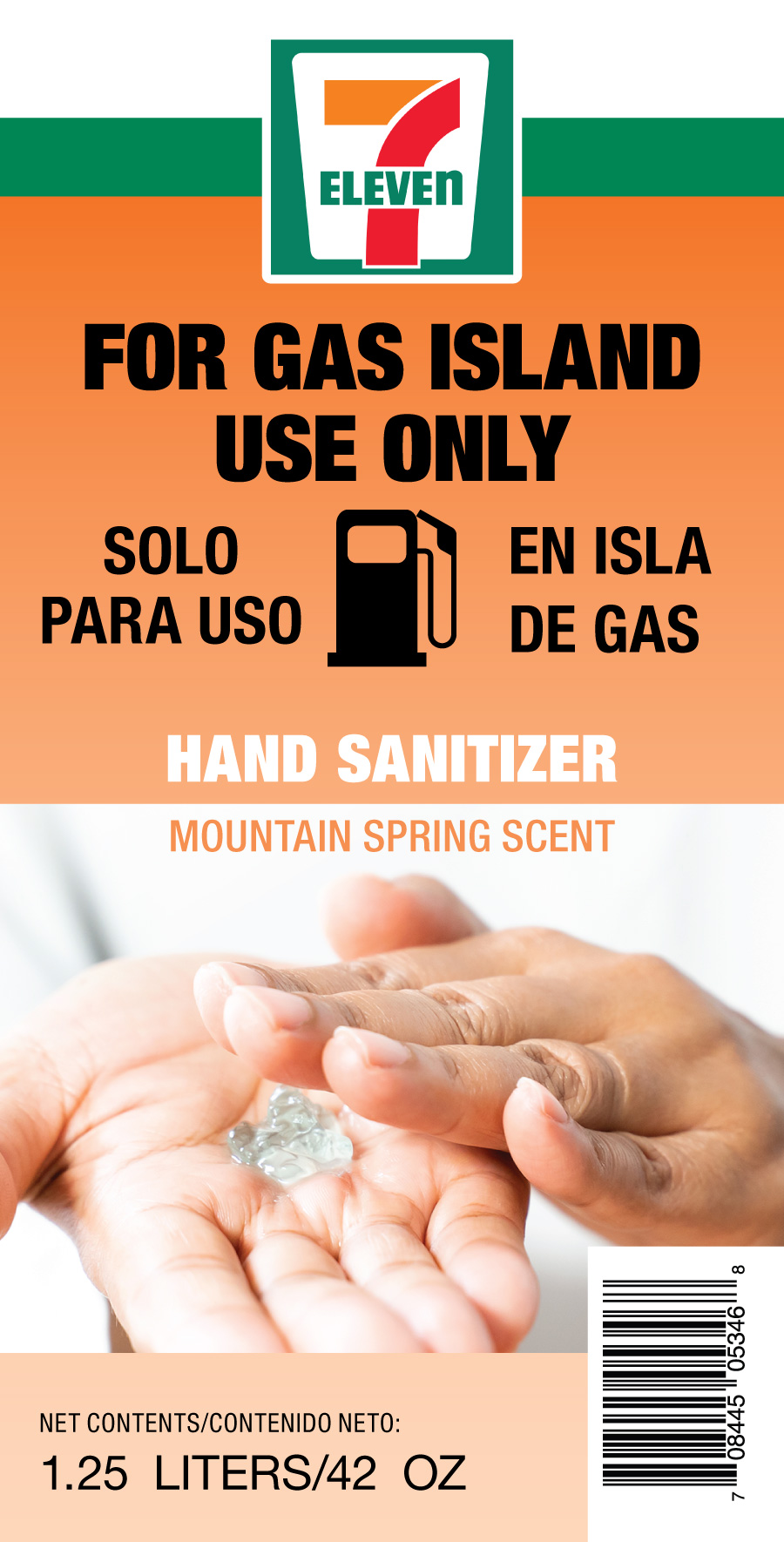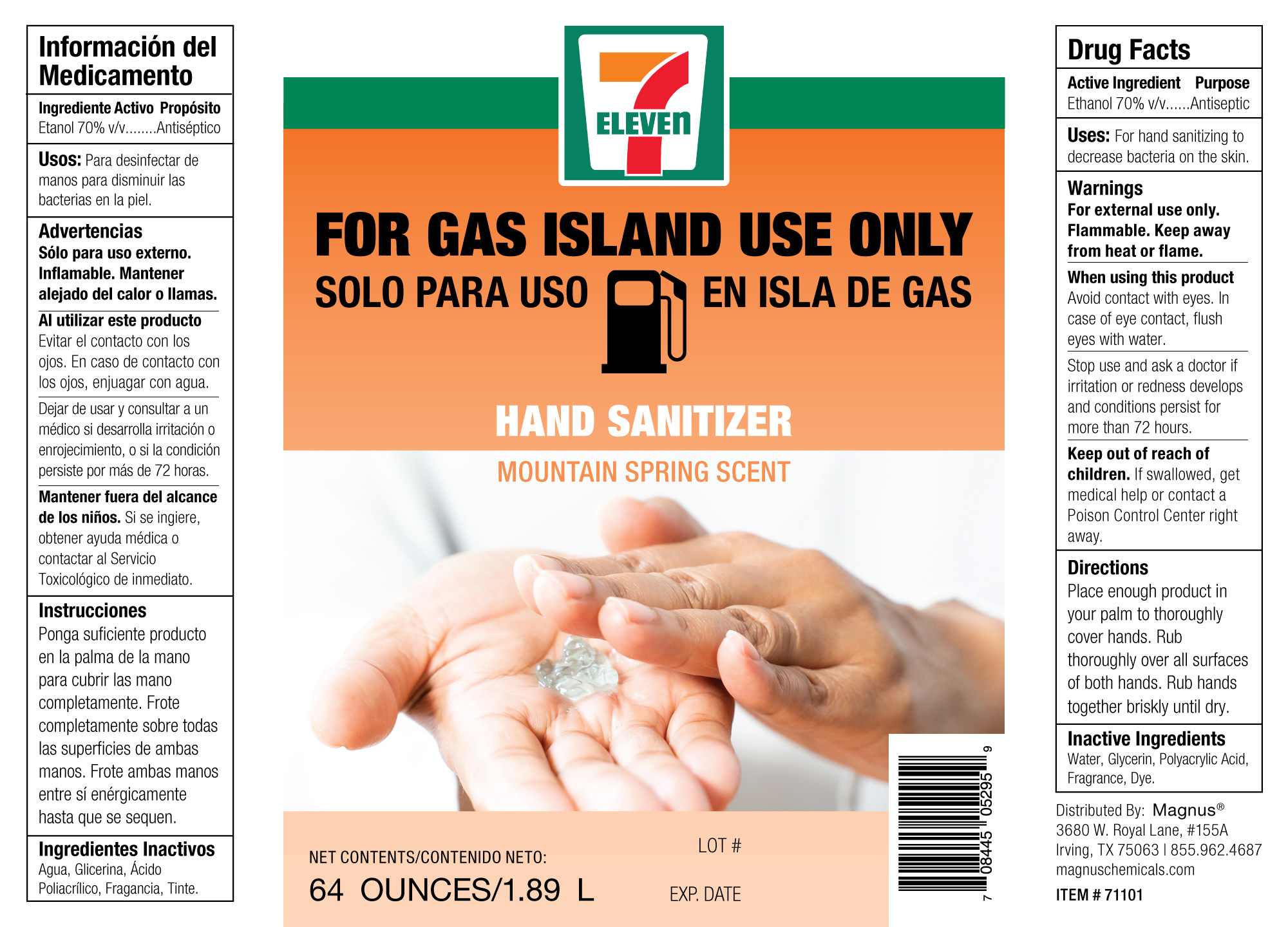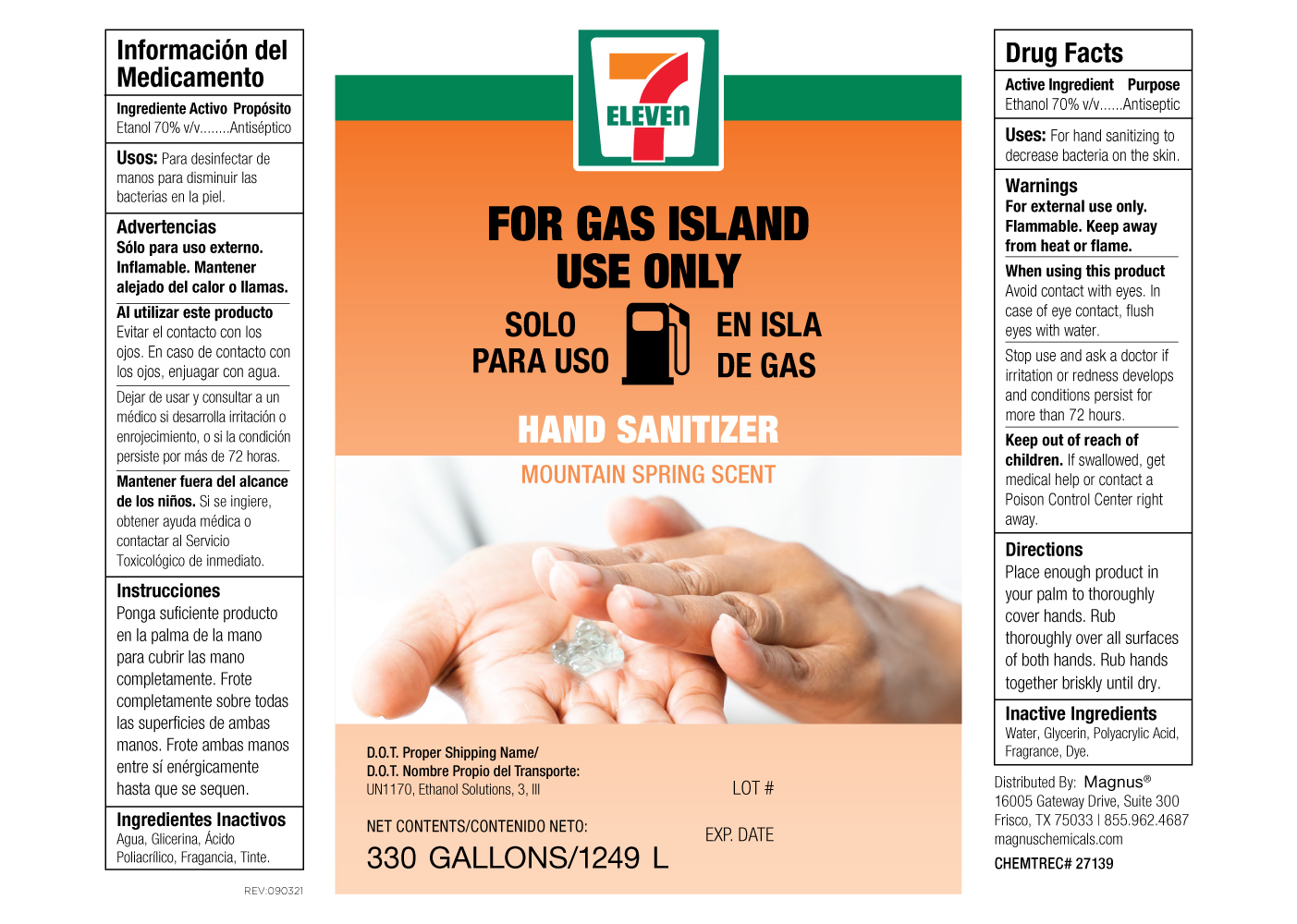 DRUG LABEL: 7 ELEVEN HAND SANITIZER MOUNTAIN SPRING SCENT
NDC: 81122-139 | Form: GEL
Manufacturer: Magnus Procurement & Logistics Solution, Inc.
Category: otc | Type: HUMAN OTC DRUG LABEL
Date: 20220919

ACTIVE INGREDIENTS: ALCOHOL 70 mL/100 mL
INACTIVE INGREDIENTS: WATER; FD&C BLUE NO. 1; FRAGRANCE CLEAN ORC0600327; METHACRYLIC ACID AND ETHYL ACRYLATE COPOLYMER; GLYCERIN; FD&C YELLOW NO. 5

27139 Magnus

Active Ingredient Purpose

Ethanol 70% v/v........Antiseptic

Warnings

For external use only. Flammable. Keep away from heat or flame.

When using this product

Avoid contact with eyes. In case of eye contacy, flush eyes with water.

Stop use and ask a doctor if irritaiton or redness develops and conditions persist for more than 72 hours.

KEEP OUT OF REACH OF CHILDREN

Keep our ot reach of children. If swallowed, get medical help or contact a Poison Control Center right away.

Inactive Ingredients

Water, Glycerin, Polyacrylic Acid, Frangrance, Dye.

PURPOSE

Antiseptic, Hand Sanitizer

Stop use and ask a doctor if irritation or redness develops and conditions persist for more than 72 hours.

INDICATIONS AND USAGE

Uses: For hand sanitizing to decrease bacteria on the skin.

Directions

Place enough product in your palm to thoroughly cover hands. Rub thoroughly over all surfaces of both hands. Rub hands together briskly until dry.

PACKAGE LABEL

64 ounce 81122-139-16

PACKAGE LABEL

1.25 Liters 81122-139-25

1.25 Liters 81122139-25 Back Label

PACKAGE LABEL

330 G 81122-139-33